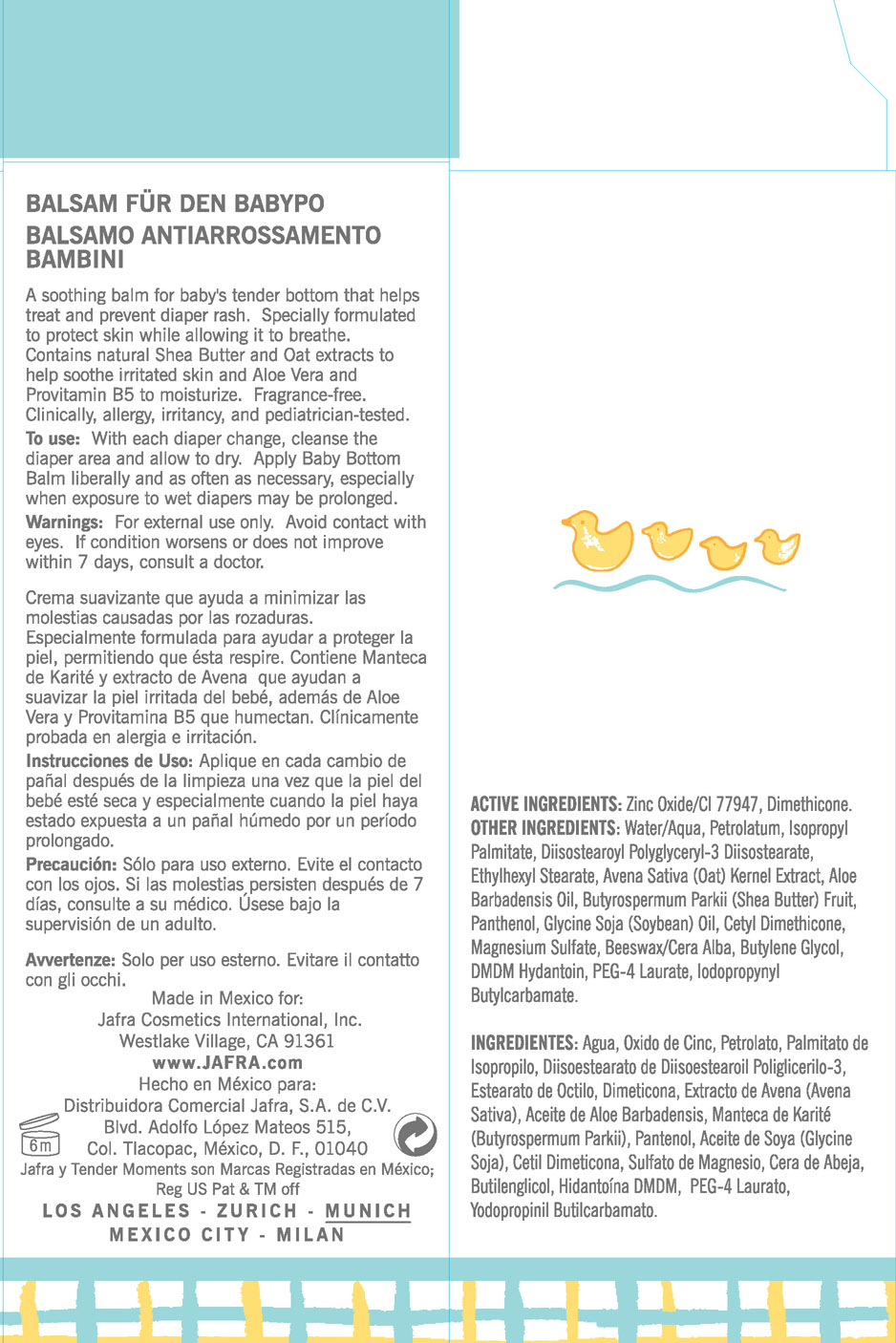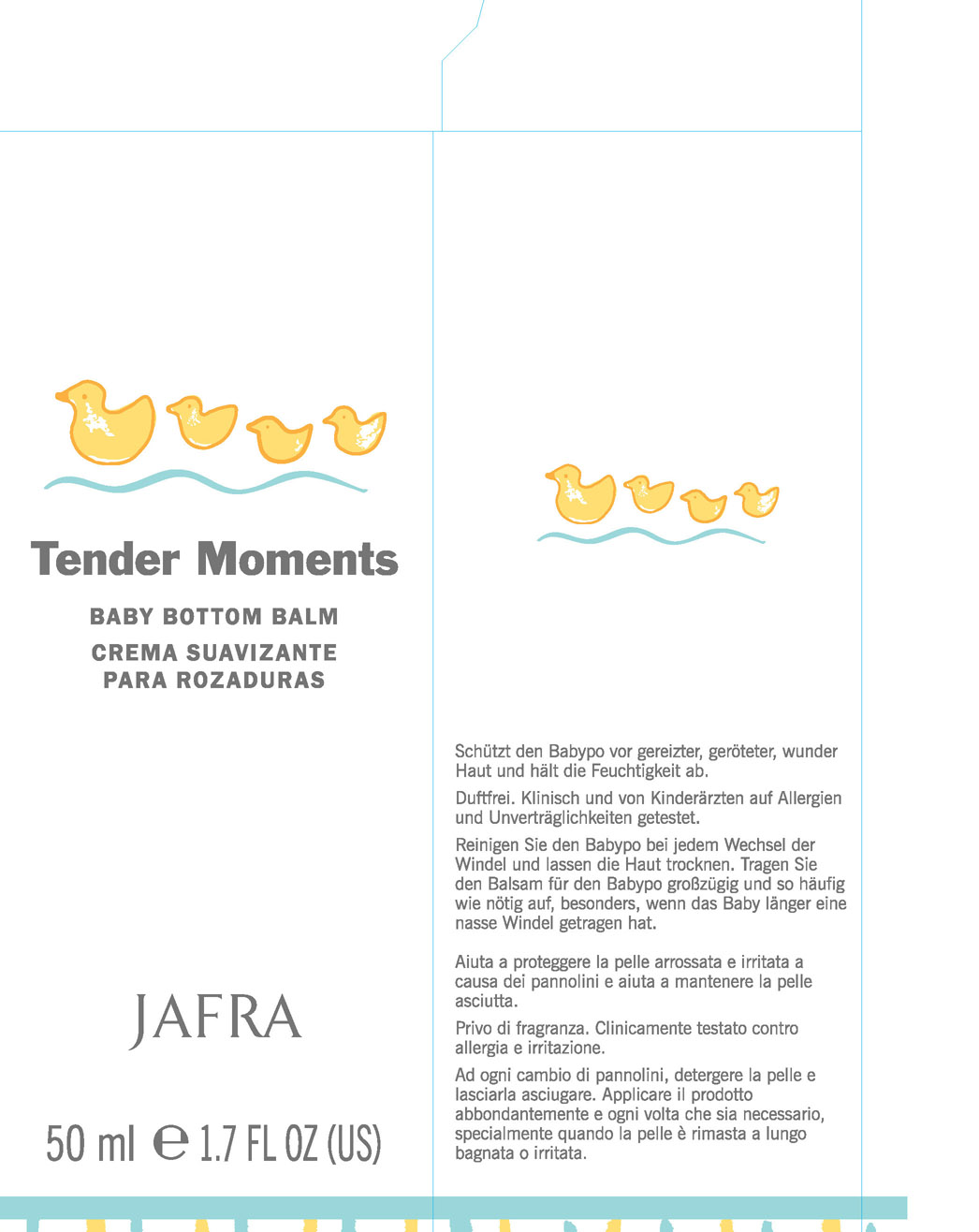 DRUG LABEL: Tender Moments
NDC: 68828-095 | Form: CREAM
Manufacturer: JAFRA COSMETICS INTERNATIONAL
Category: otc | Type: HUMAN OTC DRUG LABEL
Date: 20190523

ACTIVE INGREDIENTS: ZINC OXIDE 10 g/100 mL; DIMETHICONE 2 g/100 mL
INACTIVE INGREDIENTS: WATER; PETROLATUM; ISOPROPYL PALMITATE; OAT; PANTHENOL; SOYBEAN OIL; CETOSTEARYL ALCOHOL; MAGNESIUM SULFATE, UNSPECIFIED FORM; WHITE WAX; BUTYLENE GLYCOL; DMDM HYDANTOIN; PEG-4 LAURATE; IODOPROPYNYL BUTYLCARBAMATE

Tender moments Baby Bottom Balm

Active Ingredients: Zinc Oxide/CI77947, Dimethicone

PURPOSE

Soothing balm for baby's tender bottom that helps treat and prevent diaper rash.

KEEP OUT OF REACH OF CHILDREN

No Such information

INDICATIONS AND USAGE

If condition worsens or does not improve within 7 days, consult a doctor.

WARNINGS

For external use only. Avoid contact with eyes

DOSAGE AND ADMINISTRATION

To use: With each diaper change, cleanse the diaper area and and allow to dry. Apply baby bottom balm liberally, especially when exposure to wet diapers may be prolonged.

INACTIVE INGREDIENT

Other ingredients: Water/aqua, petrolatum, Diisostearoyl Polyglyceryl-3 Diisostearate, Ethylhexyl stearate, Avena Sativa (Oat) Kernel Extract, Aloe Barbadensis Oil, Butyrospermum Parkii (Shea Butter) Fruit, Panthenol, Glycine Soja (Soybean) Oil. Cetyl Dimethicone, Magnesium Sulfate, Beeswax/Cera Alba, Butylene Glycol, DMDM Hydantoin, PEG-4 Laurate, Iodopropynyl Butylcarbamate.

PACKAGE LABEL

Tender Moments

Baby Bottom Balm

Crema Suavizante para Rozaduras

Jafra

50 ml 1.7 fl. oz